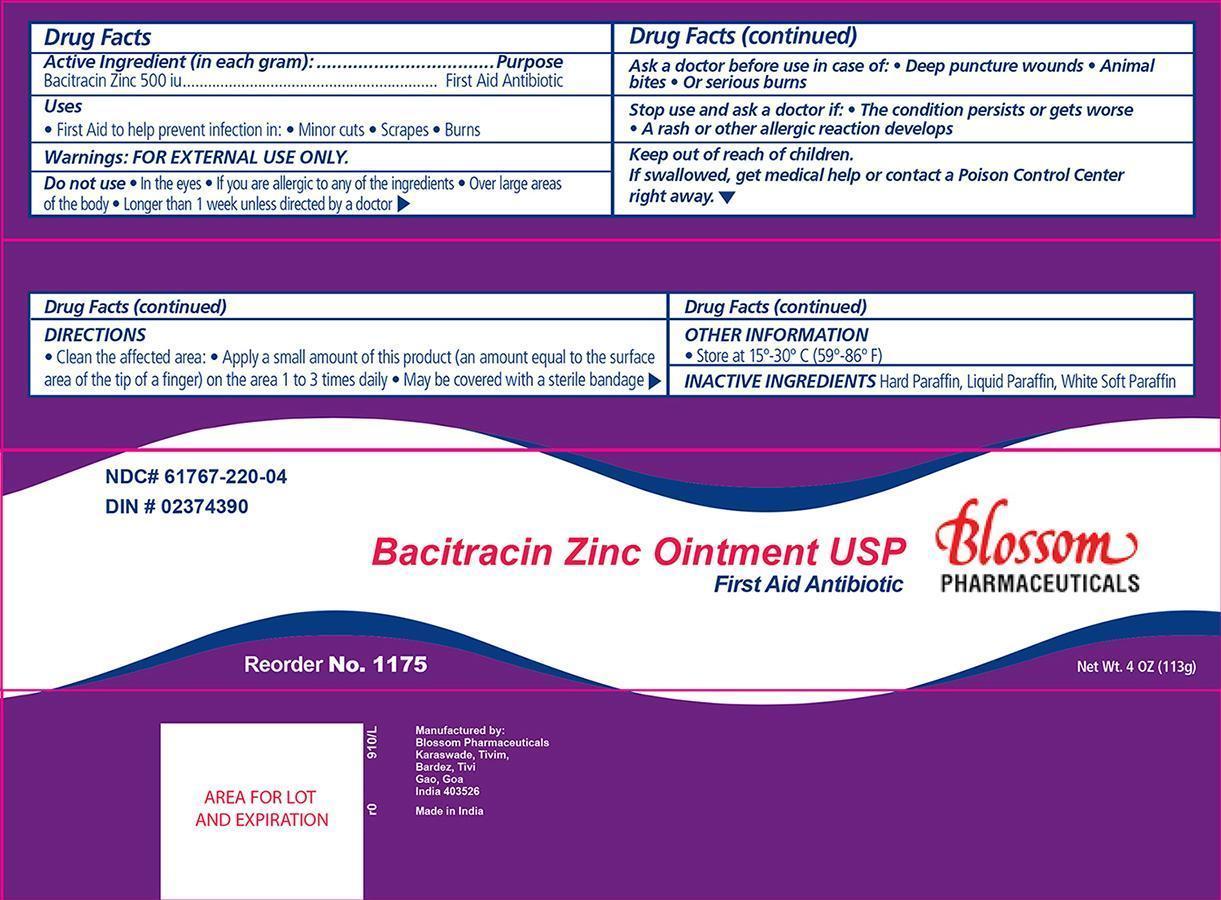 DRUG LABEL: Bacitracin Zinc
NDC: 61767-220 | Form: OINTMENT
Manufacturer: Blossom Pharmaceuticals
Category: otc | Type: HUMAN OTC DRUG LABEL
Date: 20140514

ACTIVE INGREDIENTS: BACITRACIN ZINC 500 [USP'U]/1 g
INACTIVE INGREDIENTS: PETROLATUM; LIGHT MINERAL OIL; MINERAL OIL

Bacitracin Zinc Ointment

Active ingredient Purpose
Bacitracin Zinc 500 Units Antibiotic

Warnings:

For external use only

Dosage & Administration

clean the affected areas
apply a small amount of product (an amount equal to the surface area of the tip of the finger) on the area 1 to 3 times daily
may be covered with a sterile bandage

Indications & Usage

- if you are allergic to any of the ingredients
- in the eyes
- over large areas of the body
- longer than 1 week unless directed by a doctor

KEEP OUT OF REACH OF CHILDREN

If swallowed, get medical help or contact a Poison Control Center right away

Purpose:

First aid to help prevent infection in:

- Minor cuts
- scrapes
- burns

Ask a doctor before use:

- in case of deep or puncture wounds
- animal bites
- serious burns

Other information

- store at controlled room temperature 15°-30° C (59°-86° F)

Stop Use and ask a doctor if

- the condition persists or gets worse, or if a rash or other allergic reaction develops.

Inactive ingredients

Hard Paraffin, Liquid Paraffin, White Soft Paraffin

Principal Display Panel

Blossom Pharmaceuticals Bacitracin Zinc Ointment:

bacitracin zinc.jpg